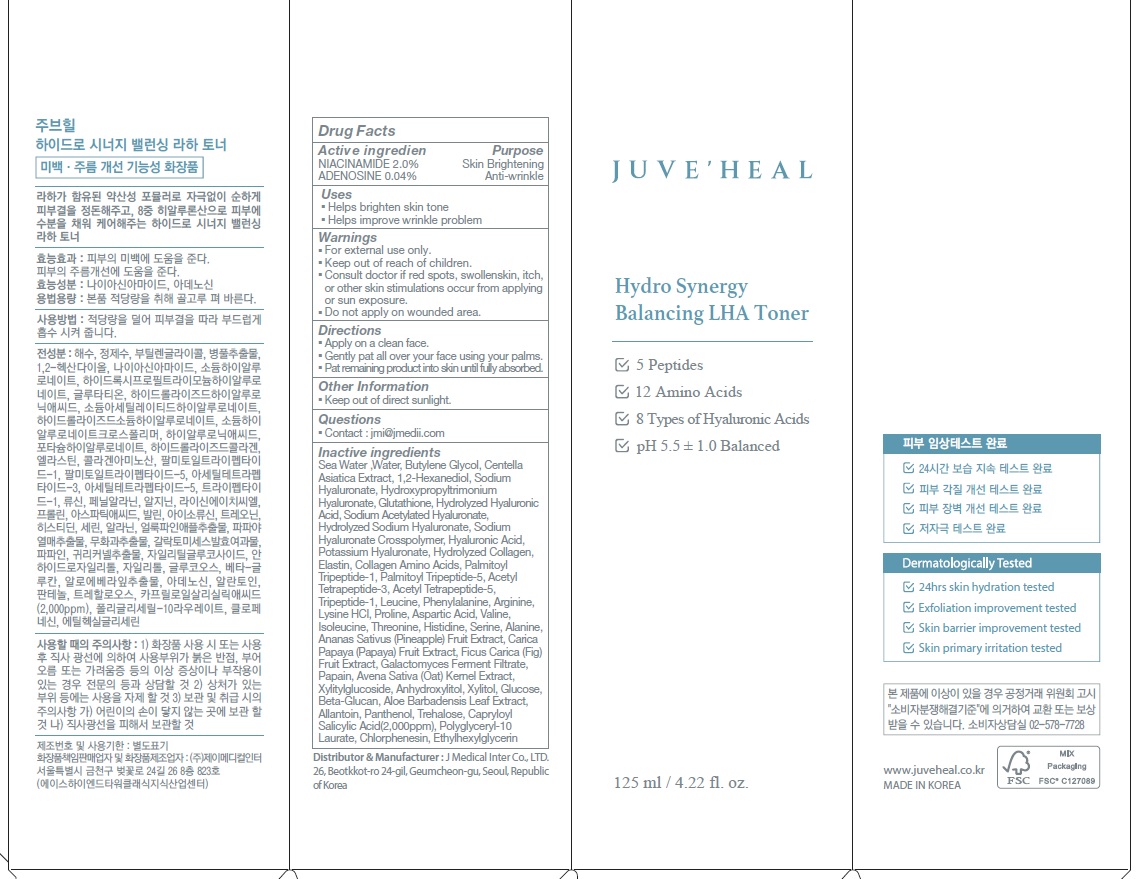 DRUG LABEL: JUVEHEAL Hydro Synergy Balancing LHA Toner
NDC: 81689-050 | Form: LIQUID
Manufacturer: J MEDICAL Inter Co., Ltd.
Category: otc | Type: HUMAN OTC DRUG LABEL
Date: 20220816

ACTIVE INGREDIENTS: NIACINAMIDE 2.0 g/100 mL; ADENOSINE 0.04 g/100 mL
INACTIVE INGREDIENTS: Water; Butylene Glycol; 1,2-Hexanediol

ACTIVE INGREDIENTS

NIACINAMIDE 2.0%
ADENOSINE 0.04%

INACTIVE INGREDIENTS

Sea Water, Water, Butylene Glycol, Centella Asiatica Extract, 1,2-Hexanediol, Sodium Hyaluronate, Hydroxypropyltrimonium Hyaluronate, Glutathione, Hydrolyzed Hyaluronic Acid, Glutathione, Hydrolyzed Hyaluronic Acid, Sodium Acetylated Hyaluronate, Hydrolyzed Sodium Hyaluronate, Sodium Hyaluronate Crosspolymer, Hyaluronic Acid, Potassium Hyaluronate, Hydrolyzed Collagen, Elastin, Collagen Amino Acids, Palmitoyl Tripeptide-1, Palmitoyl Tripeptide-5, Acetyl Tetrapeptide-3, Acetyl Tetrapeptide-5, Tripeptide-1, Leucine, Phenylalanine, Arginine, Lysine HCl, Proline, Aspartic Acid, Valine, Isoleucine, Threonine, Histidine, Serine, Alanine, Ananas Sativus (Pineapple) Fruit Extract, Carica Papaya (Papaya) Fruit Extract, Ficus Carica (Fig) Fruit Extract, Galactomyces Ferment Filtrate, Papain, Avena Sativa (Oat) Kernel Extract, Xylitylglucoside, Anhydroxylitol, Xylitol, Glucose, Beta-Glucan, Aloe Barbadensis Leaf Extract, Allantoin, Panthenol, Trehalose, Capryloyl Salicylic Acid(2,000ppm), Polyglyceryl-10 Laurate, Chlorphenesin, Ethylhexylglycerin

PURPOSE

Skin Brightening
Anti-wrinkle

WARNINGS

■ For external use only.
■ Keep out of reach of children.
■ Consult doctor if red spots, swollen skin, itch, or other skin stimulations occur from applying or sun exposure.
■ Do not apply on wounded area.

KEEP OUT OF REACH OF CHILDREN

Uses

■ Helps brighten skin tone
■ Helps improve wrinkle problem

Directions

■ Apply on a clean face.
■ Gently pat all over your face using your palms.
■ Pat remaining product into skin until fully absorbed.

Other information

■ Keep out of direct sunlight.

QUESTIONS

■ Contact : jmi@jmedii.com